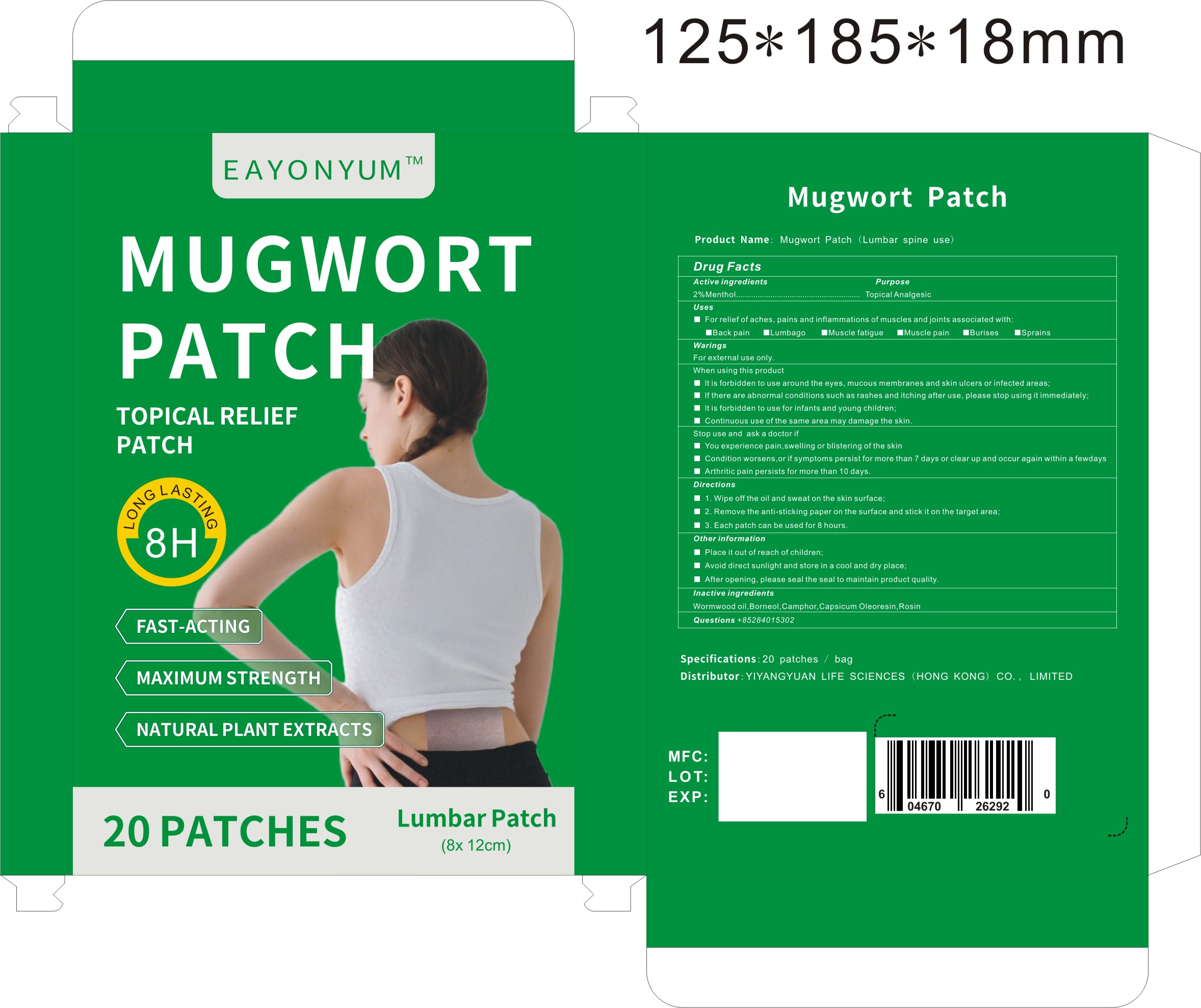 DRUG LABEL: Mugwort Patch (Lumbar spine use)
NDC: 87267-003 | Form: PATCH
Manufacturer: YIYANGYUAN LIFE SCIENCES (HONG KONG) CO., LIMITED
Category: otc | Type: HUMAN OTC DRUG LABEL
Date: 20260104

ACTIVE INGREDIENTS: MENTHOL 2 g/100 g
INACTIVE INGREDIENTS: ROSIN; BORNEOL; CAPSICUM OLEORESIN; CAMPHOR, (-)-; WORMWOOD OIL

87267-003-Mugwort Patch (Lumbar spine use)

ACTIVE INGREDIENT

Uiuurdolo
Active ingredients
2%Menthol..........
Purpose
Topical Analgesic

Uses
For relief of aches, pains and inflammations of muscles and joints associated with:
Back pain Lumbago
Muscle fatigue
Muscle pain
Burises
ISprains

Place it out of reach of children;

WARNINGS

WaringsFor external use only.

When using this product
It is forbidden to use around the eyes,mucous membranes and skin ulcers or infected areas;
If there are abnormal conditions such as rashes and itching after use, please stop using it immediately;It is forbidden to use for infants and young children;
I Continuous use of the same area may damage the skin.

Directions
1. Wipe off the oil and sweat on the skin surface;
2.Remove the anti-sticking paper on the surface and stick it on the target area;
3.Each patch can be used for 8 hours.

Inactive ingredients
Wormwood oil,Borneol,Camphor,Capsicum Oleoresin,Rosin